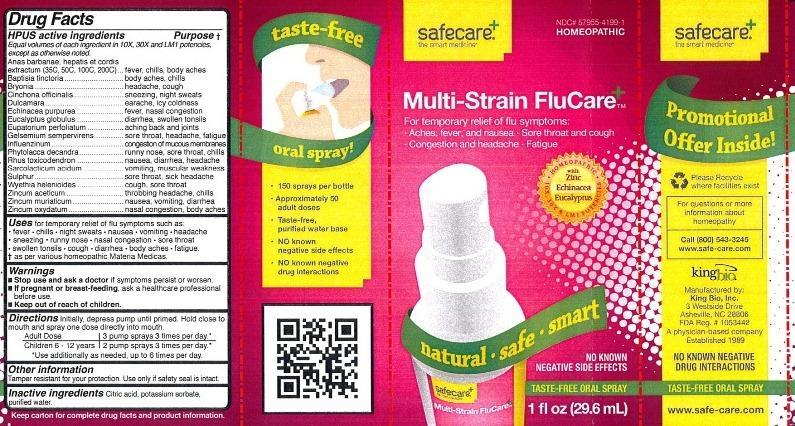 DRUG LABEL: Multi-Strain FluCare
NDC: 57955-4199 | Form: LIQUID
Manufacturer: King Bio Inc.
Category: homeopathic | Type: HUMAN OTC DRUG LABEL
Date: 20121017

ACTIVE INGREDIENTS: CAIRINA MOSCHATA HEART/LIVER AUTOLYSATE 35 [hp_C]/29.6 mL; BAPTISIA TINCTORIA ROOT 10 [hp_X]/29.6 mL; BRYONIA ALBA ROOT 10 [hp_X]/29.6 mL; CINCHONA OFFICINALIS BARK 10 [hp_X]/29.6 mL; SOLANUM DULCAMARA TOP 10 [hp_X]/29.6 mL; ECHINACEA PURPUREA 10 [hp_X]/29.6 mL; EUCALYPTUS GLOBULUS LEAF 10 [hp_X]/29.6 mL; EUPATORIUM PERFOLIATUM FLOWERING TOP 10 [hp_X]/29.6 mL; GELSEMIUM SEMPERVIRENS ROOT 10 [hp_X]/29.6 mL; INFLUENZA A VIRUS 10 [hp_X]/29.6 mL; INFLUENZA B VIRUS 10 [hp_X]/29.6 mL; PHYTOLACCA AMERICANA ROOT 10 [hp_X]/29.6 mL; TOXICODENDRON PUBESCENS LEAF 10 [hp_X]/29.6 mL; LACTIC ACID, L- 10 [hp_X]/29.6 mL; SULFUR 10 [hp_X]/29.6 mL; WYETHIA HELENIOIDES ROOT 10 [hp_X]/29.6 mL; ZINC ACETATE ANHYDROUS 10 [hp_X]/29.6 mL; ZINC CHLORIDE 10 [hp_X]/29.6 mL; ZINC OXIDE 10 [hp_X]/29.6 mL
INACTIVE INGREDIENTS: WATER; CITRIC ACID MONOHYDRATE; POTASSIUM SORBATE

Multi-Strain FluCare

Active Ingredients

HPUS active ingredients

Equal volumes of each ingredient in 10X, 30X and LM1 potencies, except as otherwise noted. Anas barbariae, hepatis et cordis extractum (35C, 50C, 100C, 200C)

Anas barbariae, hepatis et cordis extractum, Baptisia tinctoria, Bryonia, Cinchona officinalis, Dulcamara, Echinacea purpurea, Eucalyptus globulus, Eupatorium perfoliatum, Gelsemium sempervirens, Influenzinum, Phytolacca decandra, Rhus toxicodendron, Sarcolacticum acidum, Sulphur, Wyethia helenioides, Zincum aceticum, Zincum muriaticum, Zincum oxydatum.

Inactive Ingredients

Purified water, potassium sorbate and citric acid.

Purpose

Drug Facts

HPUS active ingredients Purpose

Equal volumes of each ingredient in 10X, 30X and LM1 potencies, except as otherwise noted.

Anas barbariae, hepatis er cordis extractum (35C, 50C, 100C, 200C)..fever, chills, body aches

Baptisia tinctoria................................................................................body aches, chills

Bryonia..............................................................................................headache, cough

Cinchona officinalis............................................................................sneezing, night sweats

Dulcamara.........................................................................................earache, icy coldness

Echinacea purpurea...........................................................................fever, nasal congestion

Eucalyptus globulus...........................................................................diarrhea, swollen tonsils

Eupatorium perfoliatum......................................................................aching back and joints

Gelsemium sempervirens...................................................................sore throat, headache, fatigue

Influenzinum......................................................................................congestion of mucous membranes

Phytolacca decandra..........................................................................runny nose, sore throat, chills

Rhus toxicodendron...........................................................................nausea, diarrhea, headache

Sarcolacticum acidum.........................................................................vomiting, muscular weakness

Sulphur..............................................................................................sore throat, sick headache

Wyethia helenioides...........................................................................cough, sore throat

Zincum aceticum.................................................................................throbbing headache, chills

Zincum muriaticum..............................................................................nausea, vomiting, diarrhea

Zincum oxydatum................................................................................nasal congestion, body aches

Dosage and Administration

Directions Initially, depress pump until primed. Hold close to mouth and spray one dose directly into mouth.

Adult Dose 3 pump sprays 3 times per day.

Children 6 - 12 years 2 pump sprays 3 times per day.

Use additionally as needed, up to 6 times per day.

Warnings

- Stop use and ask a doctor if symptoms persist or worsen
- If pregnant or breast-feeding, ask a healthcare professional before use.
- Keep out of reach of children.

Other information: Tamper resistant for your protection. Use only if safety seal is intact.

Keep out of reach of children.

Indications and Usage

Uses for temporary relief of flu symptoms such as:

- fever
- chills
- night sweats
- nausea
- vomiting
- headache
- sneezing
- runny nose
- nasal congestion
- sore throat
- swollen tonsils
- cough
- diarrhea
- body aches
- fatigue

as per various homeopathic Materia Medicas.

PACKAGE LABEL

King Bio Inc.

3 Westside Drive

Asheville, NC 28806

For questions or more information about homeopathy call 800.543.3245 or www.safe-care.com